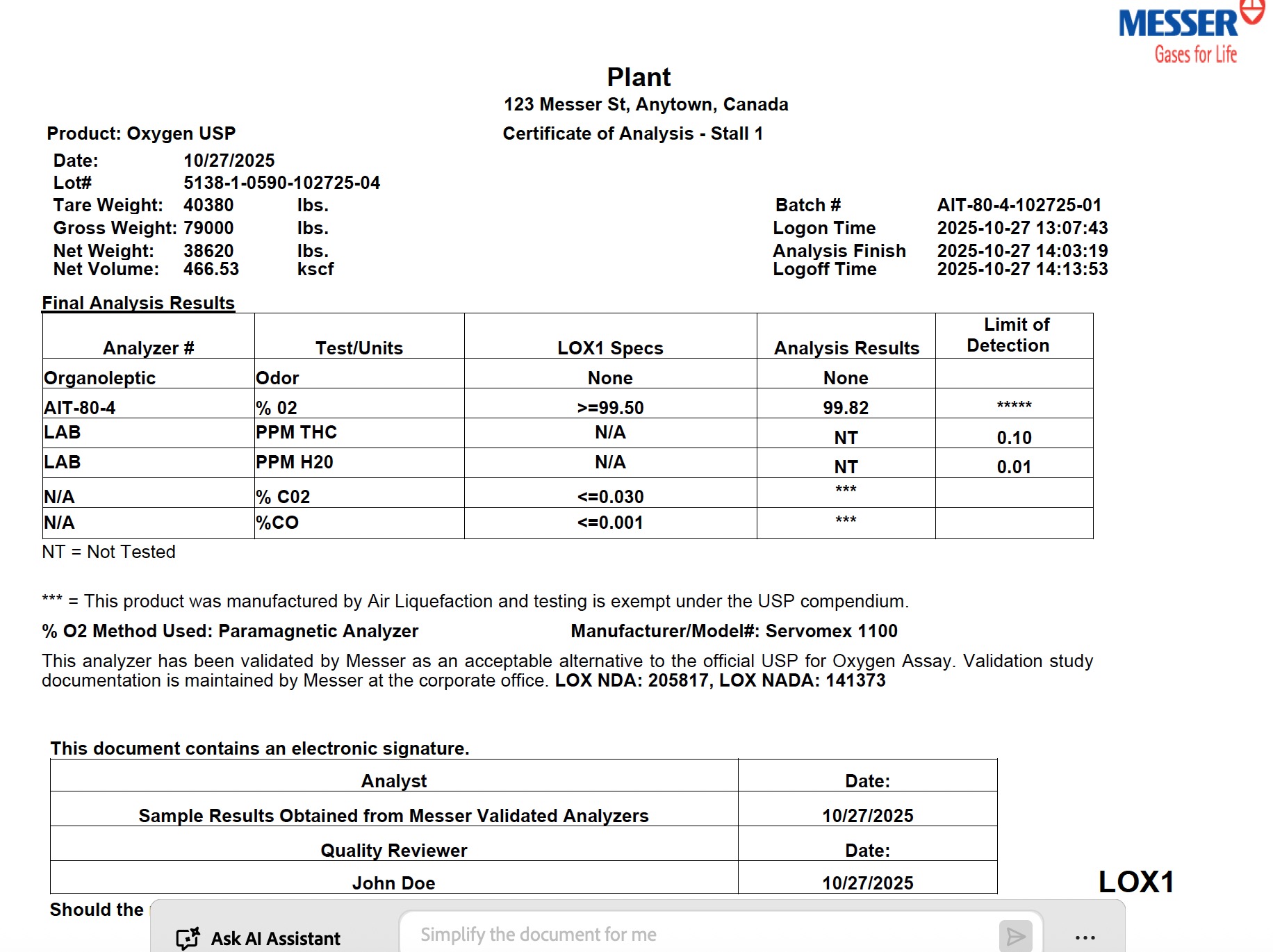 DRUG LABEL: Oxygen
NDC: 52003-011 | Form: GAS
Manufacturer: Messer Canada Inc.
Category: prescription | Type: HUMAN PRESCRIPTION DRUG LABEL
Date: 20251114

ACTIVE INGREDIENTS: OXYGEN 995 mL/1 L

Messer Canada - Oxygen USP Bulk Liquid

PACKAGE LABEL

Plant
123 Messer St, Anytown, Canada

Certificate of Analysis - Stall 1

Product: Oxygen USP
Date: 10/27/2025
Lot#: 5138-1-0590-102725-04
Tare Weight: 40380 lbs.
Gross Weight: 79000 lbs.
Net Weight: 38620 lbs.
Net Volume: 466.53 kscf

Batch #: AIT-80-4-102725-01
Logon Time: 2025-10-27 13:07:43
Analysis Finish: 2025-10-27 14:03:19
Logoff Time: 2025-10-27 14:13:53

Final Analysis Results

Analyzer #

Test/Units

LOX1 Specs

Analysis Results

Limit of Detection

Organoleptic

Odor

None

None

AIT-80-4

% O₂

≥ 99.50

99.82

*****

LAB

PPM THC

N/A

NT

0.10

LAB

PPM H₂O

N/A

NT

0.01

N/A

% CO₂

≤ 0.030

***

N/A

% CO

≤ 0.001

***

NT = Not Tested

*** = This product was manufactured by Air Liquefaction and testing is exempt under the USP compendium.

% O₂ Method Used: Paramagnetic Analyzer Manufacturer/Model#: Servomex 1100

This analyzer has been validated by Messer as an acceptable alternative to the official USP for Oxygen Assay. Validation study documentation is maintained by Messer at the corporate office. LOX NDA: 205817, LOX NADA: 141373

This document contains an electronic signature.

Analyst

Date

Sample Results Obtained from Messer Validated Analyzers

10/27/2025

Quality Reviewer

Date

John Doe

10/27/2025

Should the material not be delivered to an USP customer, the material is "Not Approved for Human Drug Use"

LOX1